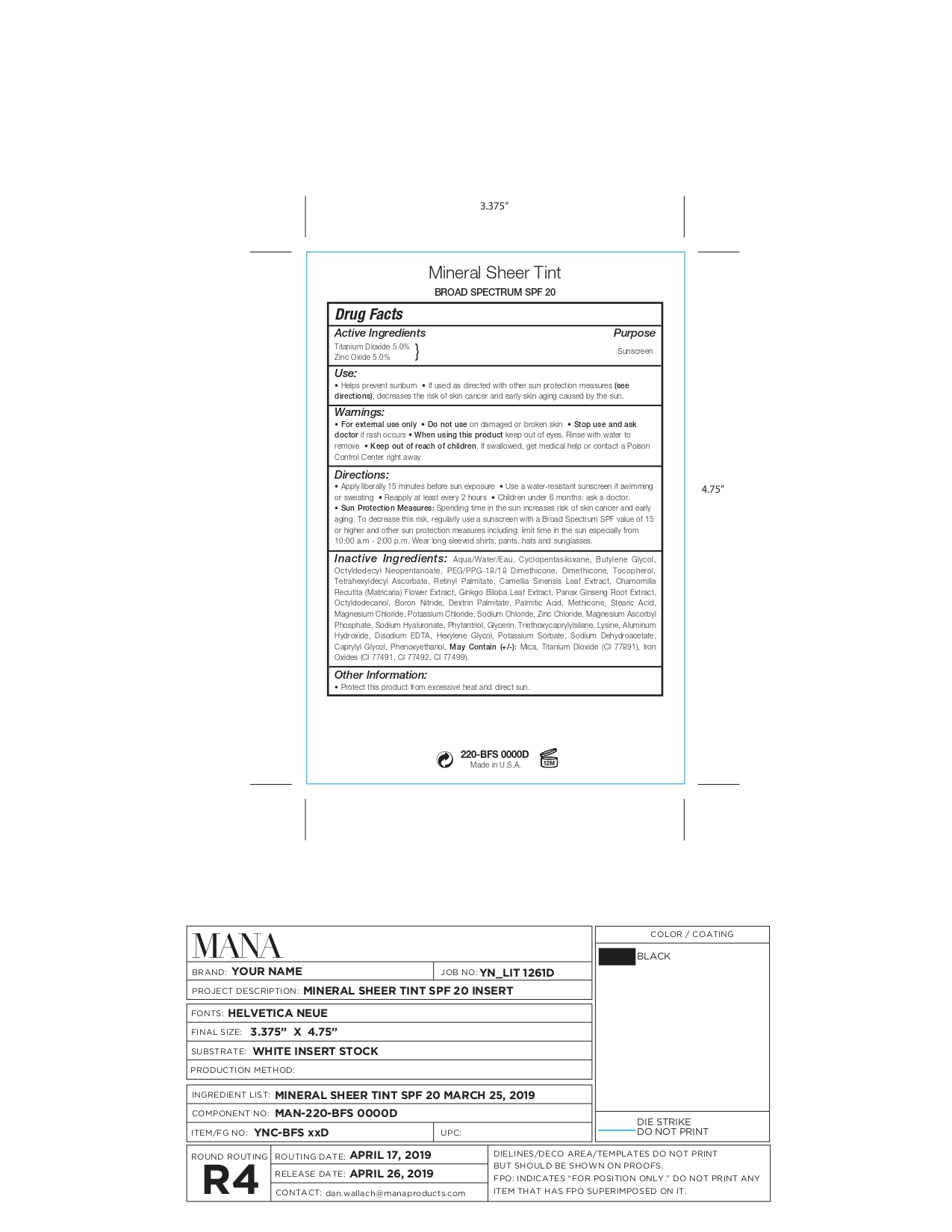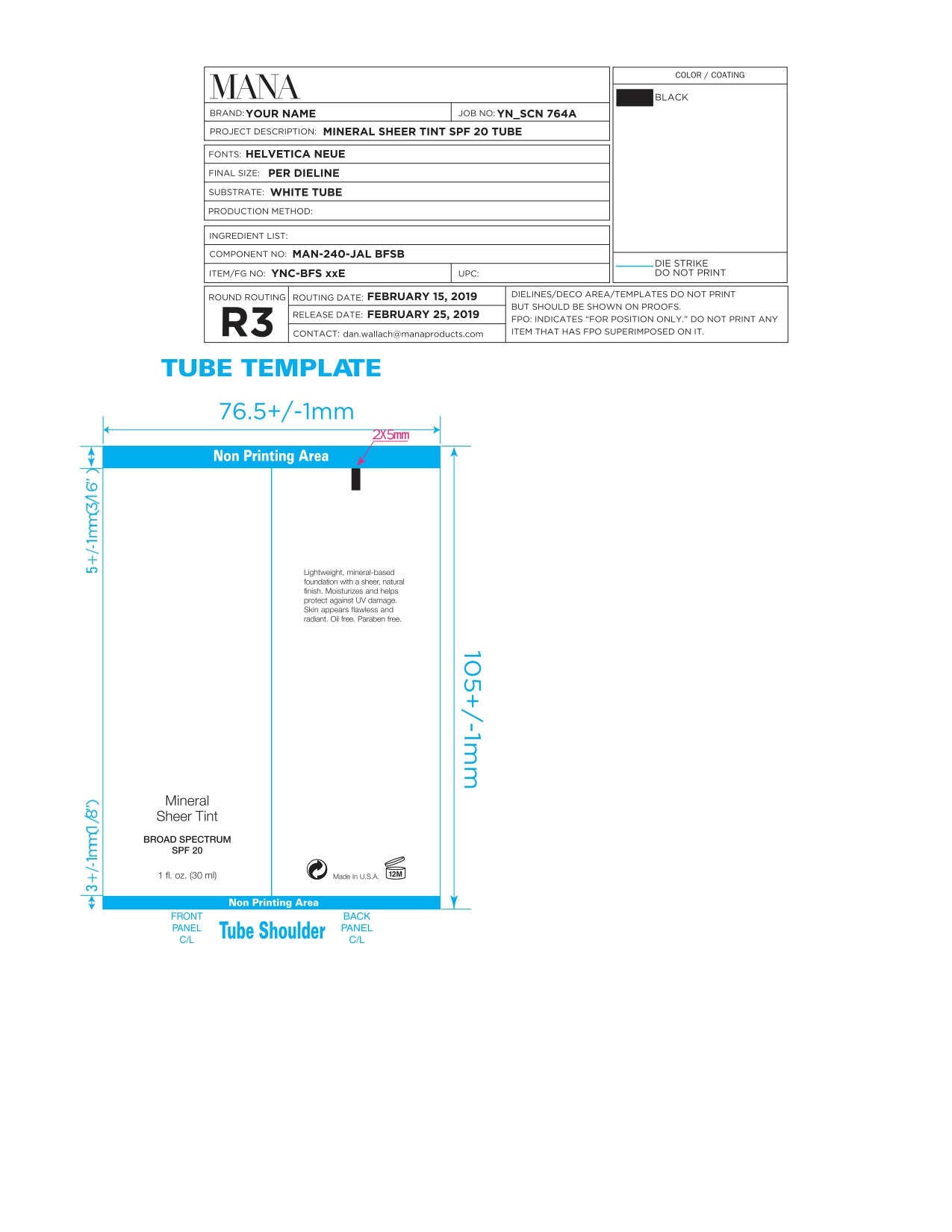 DRUG LABEL: YOUR NAME MINERAL SHEERTINT  BROAD SPECTRUM SPF 20
NDC: 59735-172 | Form: CREAM
Manufacturer: Mana Product, Inc
Category: otc | Type: HUMAN OTC DRUG LABEL
Date: 20250328

ACTIVE INGREDIENTS: ZINC OXIDE 5 g/30 mL; TITANIUM DIOXIDE 5 g/30 mL
INACTIVE INGREDIENTS: GLYCERIN; LYSINE; ALUMINUM HYDROXIDE; SODIUM DEHYDROACETATE; FERRIC OXIDE YELLOW; FERROSOFERRIC OXIDE; OCTYLDODECYL NEOPENTANOATE; TOCOPHEROL; ASIAN GINSENG; CYCLOMETHICONE 5; METHICONE (20 CST); STEARIC ACID; POTASSIUM CHLORIDE; SODIUM CHLORIDE; PHENOXYETHANOL; BORON NITRIDE; MAGNESIUM CHLORIDE; POTASSIUM SORBATE; BUTYLENE GLYCOL; PEG/PPG-18/18 DIMETHICONE; GREEN TEA LEAF; CHAMOMILE; TRIETHOXYCAPRYLYLSILANE; CAPRYLYL GLYCOL; MICA; PALMITIC ACID; WATER; GINKGO; OCTYLDODECANOL; MAGNESIUM ASCORBYL PHOSPHATE; HYALURONIC ACID (NON-ANIMAL STABILIZED); PHYTANTRIOL; DIMETHICONE; TETRAHEXYLDECYL ASCORBATE; VITAMIN A PALMITATE; DEXTRIN PALMITATE (CORN; 20000 MW); EDETATE DISODIUM; HEXYLENE GLYCOL; FERRIC OXIDE RED; ZINC CHLORIDE

YOUR NAME MINERAL SHEER TINT BROAD SPECTRUM SPF 20 Porcelain

ACTIVE INGREDIENTS

Titanium Dioxide 5.00%

Zinc Oxide 5.00%

PURPOSE

Sunscreen active

USE

Helps prevent sunburn.
If used as directed with other sun protection measures (see Directions), decreases the risk of skin cancer and early skin aging caused by the sun.

WARNINGS

- For external use only
- Do not use on damaged or broken skin
- When using this product keep out of eyes. Rinse with water to remove.

DIRECTIONS

Apply liberally 15 minutes before sun exposure.
Use water resistant sunscreen if swimming or sweating.

Reapply at least every 2 hours.

Children under 6 months: ask a doctor.
Sun Protection Measures: Spending time in the sun increases risk of skin cancer and early aging. To decrease this risk, regularly use a sunscreen with a Broad Spectrum SPF value of 15 or higher and other sun protection measures including: Limit time in the sun especially from 10:00 am - 2:00 pm. Wear long sleeved shirts, pants, hats and sunglasses.

OTHER INFORMATION

Protect this product from exessive heat and direct sun.

Stop use and ask a doctor if rash occurs.

RECENT MAJOR CHANGES

dosage & admin update

INACTIVE INGREDIENT

Water, Cyclopentasiloxane, Butylene Glycol, Titanium Dioxide, Zinc Oxide, Octyldodecyl Neopentanoate, PEG/PPG-18/18 Dimethicone, Dimethicone, Tocopherol, Tetrahexyldecyl Ascorbate, Retinyl Palmitate, Camellia Sinensis Leaf Extract, Chamomilla Recutita (Matricaria) Flower Extract, Ginkgo Biloba Leaf Extract, Panax Ginseng Root Extract, Octyldodecanol, Boron Nitride, Dextrin Palmitate, Palmitic Acid, Methicone, Stearic Acid, Magnesium Chloride, Potassium Chloride, Sodium Chloride, Zinc Chloride, Magnesium Ascorbyl Phosphate, Sodium Hyaluronate, Phytantriol, Glycerin, Triethoxycaprylylsilane, Lysine, Aluminum Hydroxide, Disodium EDTA, Hexylene Glycol, Potassium Sorbate, Sodium Dehydroacetate, Caprylyl Glycol, Phenoxyethanol

MAY CONTAIN (+/-):

Mica, Titanium Dioxide (CI 77891), Iron Oxides (CI 77491, CI 77492, CI 77499)

Keep out of reach of children. If swallowed, get medical help or contact a Poison Control Center right away.